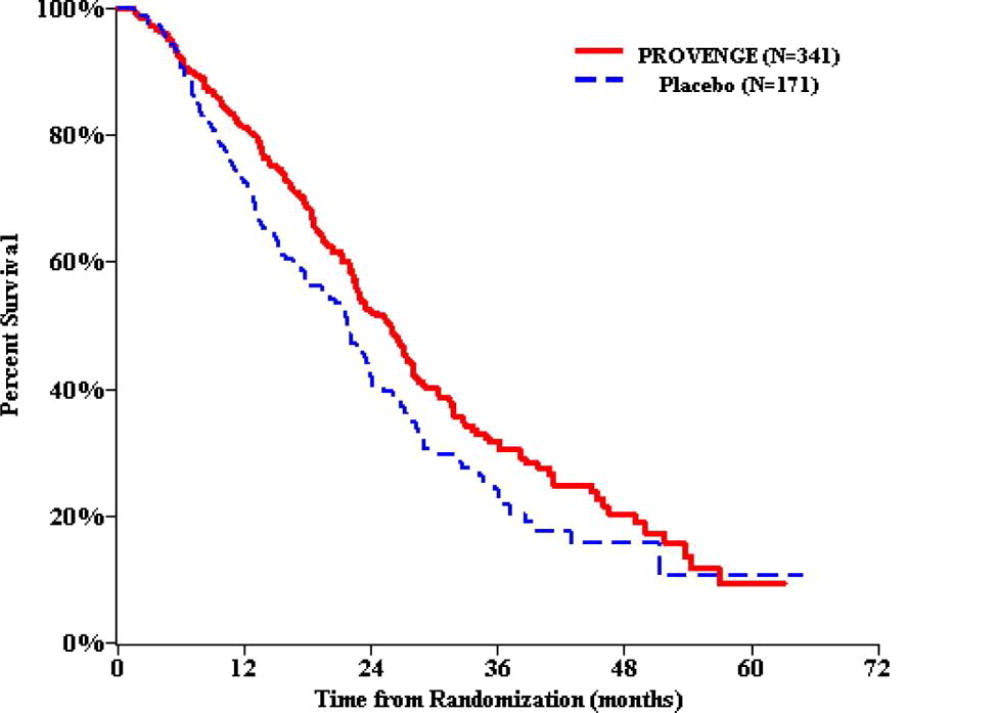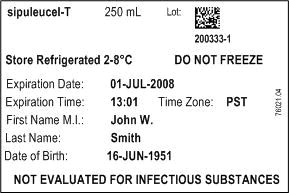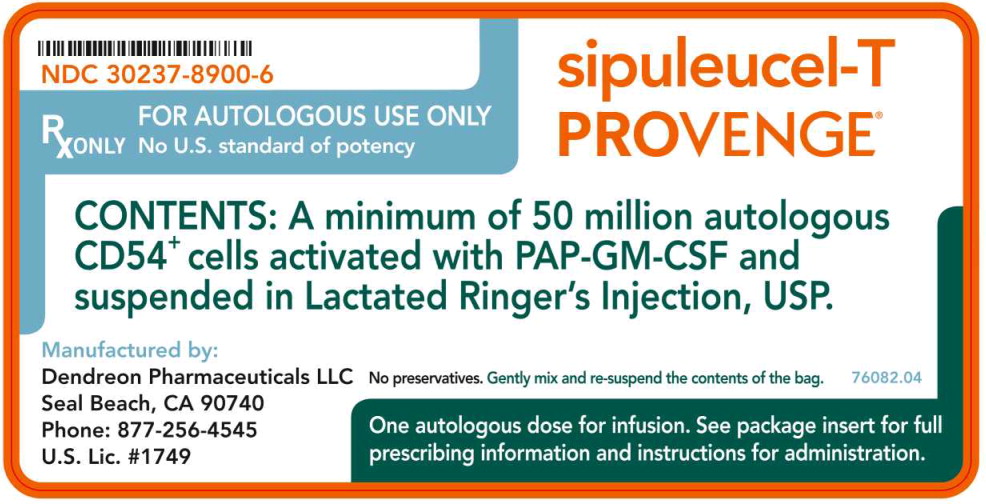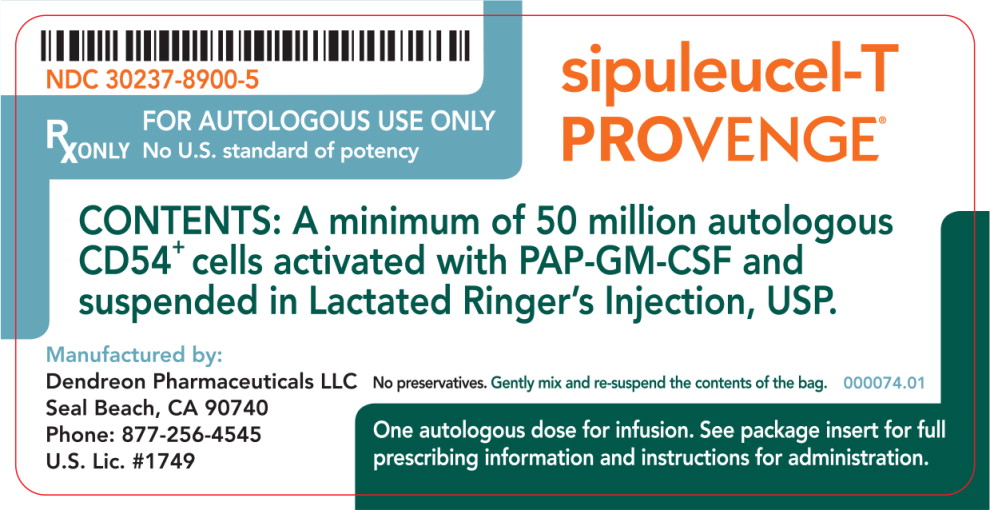 DRUG LABEL: PROVENGE
NDC: 30237-8900 | Form: INJECTION
Manufacturer: Dendreon Pharmaceuticals LLC
Category: other | Type: CELLULAR THERAPY
Date: 20251003

ACTIVE INGREDIENTS: SIPULEUCEL-T 50000000 1/1 1
INACTIVE INGREDIENTS: CALCIUM CHLORIDE; POTASSIUM CHLORIDE; WATER; SODIUM CHLORIDE; SODIUM LACTATE

HIGHLIGHTS OF PRESCRIBING INFORMATION

These highlights do not include all the information needed to use PROVENGE® (sipuleucel-T) safely and effectively. See full prescribing information for PROVENGE.
PROVENGE® (sipuleucel-T)
Suspension for Intravenous Infusion
Initial U.S. Approval: 2010

RECENT MAJOR CHANGES

Dosage and Administration
Administration (2.2) | 9/2014
Warnings and Precautions
Acute Infusion Reactions (5.1) | 10/2014
Thromboembolic Events (5.2) | 10/2014
Vascular Disorders (5.3) | 10/2014

1 INDICATIONS AND USAGE

PROVENGE is an autologous cellular immunotherapy indicated for the treatment of asymptomatic or minimally symptomatic metastatic castrate-resistant (hormone-refractory) prostate cancer. (1)

2 DOSAGE AND ADMINISTRATION

For autologous use only.

For intravenous use only.

- Administer 3 doses at approximately 2-week intervals. (2.1)
- Premedicate patients with oral acetaminophen and an antihistamine such as diphenhydramine. (2.2)
- Before infusion, confirm that the patient's identity matches the patient identifiers on the infusion bag. (2.2)
- Infuse PROVENGE intravenously over a period of approximately 60 minutes. Do Not Use a Cell Filter. (2.2)
- Interrupt or slow infusion for acute infusion reactions, depending on the severity of the reaction. (2.2)

3 DOSAGE FORMS AND STRENGTHS

Each dose of PROVENGE contains a minimum of 50 million autologous CD54^+ cells activated with PAP-GM-CSF, suspended in 250 mL of Lactated Ringer's Injection, USP. (3)

4 CONTRAINDICATIONS

None. (4)

5 WARNINGS AND PRECAUTIONS

- Acute infusion reactions may occur. If reactions occur, decrease the rate or stop the infusion and administer appropriate medical treatment. (5.1)
- Syncope and hypotension have also been observed. Closely monitor patients with cardiac or pulmonary conditions. (5.1)
- PROVENGE should be used with caution in patients with risk factors for thromboembolic events. (5.2)
- PROVENGE is not tested for transmissible infectious diseases and may transmit diseases to health care professionals handling the product. Universal precautions should be followed. (5.4)
- Concomitant use of chemotherapy and immunosuppressive medications with PROVENGE has not been studied. (5.5)

6 ADVERSE REACTIONS

The most common adverse reactions (incidence ≥ 15%) are chills, fatigue, fever, back pain, nausea, joint ache, and headache. (6)

To report SUSPECTED ADVERSE REACTIONS, contact Dendreon Pharmaceuticals LLC at 1-877-336-3736 or FDA at 1-800-FDA-1088 or www.fda.gov/medwatch.

FULL PRESCRIBING INFORMATION

1 INDICATIONS AND USAGE

PROVENGE® (sipuleucel-T) is an autologous cellular immunotherapy indicated for the treatment of asymptomatic or minimally symptomatic metastatic castrate-resistant (hormone-refractory) prostate cancer.

2 DOSAGE AND ADMINISTRATION

For autologous use only.

For intravenous use only.

2.1 Dose

Each dose of PROVENGE contains a minimum of 50 million autologous CD54^+ cells activated with PAP-GM-CSF [ see Description (11) ].

The recommended course of therapy for PROVENGE is 3 complete doses, given at approximately 2-week intervals. In controlled clinical trials, the median dosing interval between infusions was 2 weeks (range 1 to 15 weeks); the maximum dosing interval has not been established.

If, for any reason, the patient is unable to receive a scheduled infusion of PROVENGE, the patient will need to undergo an additional leukapheresis procedure prior to continuing a course of treatment. Advise patients of this possibility prior to initiating treatment.

2.2 Administration

- Do not use PROVENGE until confirmation of product release is received from Dendreon.
- Dendreon will send the Final Product Disposition Notification form containing the patient identifiers, expiration date and time, and the disposition status (approved for infusion or rejected), to the infusion site. Infusion must begin prior to the expiration date and time indicated on the Final Product Disposition Notification form and Product Label. Do not use expired PROVENGE. Keep the sealed, patient-specific PROVENGE infusion bag within the insulated polyurethane container inside the outer cardboard shipping box until the time of administration.
- To minimize potential acute infusion reactions, premedicate the patients orally with acetaminophen and an antihistamine, such as diphenhydramine, approximately 30 minutes prior to administration of PROVENGE.

Administration steps:

1. Remove the infusion bag from the insulated polyurethane container and inspect the bag for signs of leakage or external damage. Contents of the bag will be clear to opaque, with a white to red color, including shades of off-white, cream, light yellow and orange. Remove the infusion bag from the insulated polyurethane container and inspect the bag for signs of leakage or external damage. Contents of the bag will be clear to opaque, with a white to red color, including shades of off-white, cream, light yellow and orange.
2. Gently mix and resuspend the contents of the bag, inspecting for clumps and clots. Small clumps of cellular material should disperse with gentle manual mixing. Do not administer if the bag leaks during handling, is damaged, or if clumps remain in the bag.
3. Match the patient's identity with the patient identifiers on the Final Product Disposition Notification form and the PROVENGE infusion bag.
4. Infuse the entire volume of the PROVENGE infusion bag intravenously over approximately 60 minutes. Do not use a cell filter.
5. Observe the patient for acute infusion reactions for at least 30 minutes following each infusion.
  - If acute infusion reactions occur, such as chills, fatigue, fever, nausea, and joint ache, interrupt or slow the infusion and administer appropriate medical treatment as needed. In controlled clinical trials, symptoms of acute infusion reactions were treated with acetaminophen, intravenous H1 and/or H2 blockers, and low-dose intravenous meperidine.
  - If the infusion is interrupted, keep the PROVENGE infusion bag at room temperature.
  - Do not resume infusion if the PROVENGE infusion bag has been at room temperature for more than 3 hours.

3 DOSAGE FORMS AND STRENGTHS

Each dose of PROVENGE contains a minimum of 50 million autologous CD54^+ cells activated with PAP-GM-CSF, suspended in 250 mL of Lactated Ringer's Injection, USP.

4 CONTRAINDICATIONS

None.

5 WARNINGS AND PRECAUTIONS

5.1 Acute Infusion Reactions

Acute infusion reactions (reported within 1 day of infusion) may occur and include nausea, vomiting, fatigue, fever, rigor or chills, respiratory events (dyspnea, hypoxia, and bronchospasm), syncope, hypotension, hypertension, and tachycardia. Acute infusion reactions (reported within 1 day of infusion) may occur and include nausea, vomiting, fatigue, fever, rigor or chills, respiratory events (dyspnea, hypoxia, and bronchospasm), syncope, hypotension, hypertension, and tachycardia.

In controlled clinical trials, 71.2% of patients in the PROVENGE group developed an acute infusion reaction. The most common events (≥ 20%) were chills, fever, and fatigue. In 95.1% of patients reporting acute infusion reactions, the reactions were mild or moderate. Fevers and chills generally resolved within 2 days (71.9% and 89%, respectively). In controlled clinical trials, 71.2% of patients in the PROVENGE group developed an acute infusion reaction. The most common events (≥ 20%) were chills, fever, and fatigue. In 95.1% of patients reporting acute infusion reactions, the reactions were mild or moderate. Fevers and chills generally resolved within 2 days (71.9% and 89%, respectively).

In controlled clinical trials, severe (Grade 3) acute infusion reactions were reported in 3.5% of patients in the PROVENGE group. Reactions included chills, fever, fatigue, asthenia, dyspnea, hypoxia, bronchospasm, dizziness, headache, hypertension, muscle ache, nausea, and vomiting. The incidence of severe events was greater following the second infusion (2.1% vs. 0.8% following the first infusion), and decreased to 1.3% following the third infusion. Some (1.2%) patients in the PROVENGE group were hospitalized within 1 day of infusion for management of acute infusion reactions. No Grade 4 or 5 acute infusion reactions were reported in patients in the PROVENGE group. In controlled clinical trials, severe (Grade 3) acute infusion reactions were reported in 3.5% of patients in the PROVENGE group. Reactions included chills, fever, fatigue, asthenia, dyspnea, hypoxia, bronchospasm, dizziness, headache, hypertension, muscle ache, nausea, and vomiting. The incidence of severe events was greater following the second infusion (2.1% vs. 0.8% following the first infusion), and decreased to 1.3% following the third infusion. Some (1.2%) patients in the PROVENGE group were hospitalized within 1 day of infusion for management of acute infusion reactions. No Grade 4 or 5 acute infusion reactions were reported in patients in the PROVENGE group.

Closely monitor patients with cardiac or pulmonary conditions. In the event of an acute infusion reaction, decrease the infusion rate or stop the infusion, depending on the severity of the reaction. Administer appropriate medical treatment as needed. [ ] Closely monitor patients with cardiac or pulmonary conditions. In the event of an acute infusion reaction, decrease the infusion rate or stop the infusion, depending on the severity of the reaction. Administer appropriate medical treatment as needed. [ See Dosage and Administration (2.2) ]

5.2 Thromboembolic Events

Thromboembolic events, including deep venous thrombosis and pulmonary embolism, can occur following infusion of PROVENGE. The clinical significance and causal relationship are uncertain. Most patients had multiple risk factors for these events. PROVENGE should be used with caution in patients with risk factors for thromboembolic events. Thromboembolic events, including deep venous thrombosis and pulmonary embolism, can occur following infusion of PROVENGE. The clinical significance and causal relationship are uncertain. Most patients had multiple risk factors for these events. PROVENGE should be used with caution in patients with risk factors for thromboembolic events.

5.3 Vascular Disorders

: In controlled clinical trials, cerebrovascular events (hemorrhagic and ischemic strokes) were observed in 3.5% of patients in the PROVENGE group compared with 2.6% of patients in the control group. In the postmarketing setting, cerebrovascular events, including transient ischemic attacks, have been observed following infusion of Provenge. The clinical significance and causal relationship are uncertain. Most patients had multiple risk factors for these events. Cerebrovascular disease: In controlled clinical trials, cerebrovascular events (hemorrhagic and ischemic strokes) were observed in 3.5% of patients in the PROVENGE group compared with 2.6% of patients in the control group. In the postmarketing setting, cerebrovascular events, including transient ischemic attacks, have been observed following infusion of Provenge. The clinical significance and causal relationship are uncertain. Most patients had multiple risk factors for these events.

: In controlled clinical trials, myocardial infarctions were observed in 0.8% of patients in the PROVENGE group compared with 0.3% of patients in the control group. In the postmarketing setting, myocardial infarctions have been observed following infusion of Provenge. The clinical significance and causal relationship are uncertain. Most patients had multiple risk factors for these events. Cardiovascular disorders: In controlled clinical trials, myocardial infarctions were observed in 0.8% of patients in the PROVENGE group compared with 0.3% of patients in the control group. In the postmarketing setting, myocardial infarctions have been observed following infusion of Provenge. The clinical significance and causal relationship are uncertain. Most patients had multiple risk factors for these events.

5.4 Handling Precautions for Control of Infectious Disease

PROVENGE is not tested for transmissible infectious diseases. Therefore, patient leukapheresis material and PROVENGE may carry the risk of transmitting infectious diseases to health care professionals handling the product. Accordingly, health care professionals should employ universal precautions when handling leukapheresis material or PROVENGE.

5.5 Concomitant Chemotherapy or Immunosuppressive Therapy

Use of either chemotherapy or immunosuppressive agents (such as systemic corticosteroids) given concurrently with the leukapheresis procedure or PROVENGE has not been studied. PROVENGE is designed to stimulate the immune system, and concurrent use of immune-suppressive agents may alter the efficacy and/or safety of PROVENGE. Therefore, evaluate patients carefully to determine whether it is medically appropriate to reduce or discontinue immunosuppressive agents prior to treatment with PROVENGE.

5.6 Product Safety Testing

PROVENGE is released for infusion based on the microbial and sterility results from several tests: microbial contamination determination by Gram stain, endotoxin content, and in-process sterility with a 2-day incubation to determine absence of microbial growth. The final (7-day incubation) sterility test results are not available at the time of infusion. If the sterility results become positive for microbial contamination after PROVENGE has been approved for infusion, Dendreon will notify the treating physician. Dendreon will attempt to identify the microorganism, perform antibiotic sensitivity testing on recovered microorganisms, and communicate the results to the treating physician. Dendreon may request additional information from the physician in order to determine the source of contamination.

6 ADVERSE REACTIONS

The most common adverse reactions reported in clinical trials (≥ 15% of patients receiving PROVENGE) were chills, fatigue, fever, back pain, nausea, joint ache, and headache.

6.1 Clinical Trials Experience

Because clinical trials are conducted under widely varying conditions, adverse reaction rates observed in the clinical trials of a drug cannot be directly compared to rates in the clinical trials of another drug and may not reflect the rates observed in practice.

The safety evaluation of PROVENGE is based on 601 prostate cancer patients in the PROVENGE group who underwent at least 1 leukapheresis procedure in four randomized, controlled clinical trials. The control group (n = 303) received non-activated autologous peripheral blood mononuclear cells. Patients received 3 infusions of PROVENGE or control every other week over a period of 4 weeks.

Almost all (98.3%) patients in the PROVENGE group and 96% in the control group reported an adverse event. In 67.4% of patients in the PROVENGE group, these adverse events were mild or moderate in severity. Severe (Grade 3) and life-threatening (Grade 4) adverse events were reported in 23.6% and 4% of patients in the PROVENGE group compared with 25.1% and 3.3% of patients in the control group. Fatal (Grade 5) adverse events were reported in 3.3% of patients in the PROVENGE group compared with 3.6% of patients in the control group. The most common (≥ 2%) Grade 3-5 adverse events reported in the PROVENGE group were back pain and chills.

Serious adverse events were reported in 24% of patients in the PROVENGE group and 25.1% of patients in the control group. Serious adverse events in the PROVENGE group included acute infusion reactions [ see Warnings and Precautions (5.1) ], cerebrovascular events [ see Warnings and Precautions (5.3) ], and single case reports of eosinophilia, rhabdomyolysis, myasthenia gravis, myositis, and tumor flare.

PROVENGE was discontinued in 1.5% of patients in Study 1 due to adverse events. Some patients who required central venous catheters for treatment with PROVENGE developed infections, including sepsis. A small number of these patients discontinued treatment as a result. Monitoring for infectious sequelae in patients with central venous catheters is recommended.

Each dose of PROVENGE requires a standard leukapheresis procedure approximately 3 days prior to the infusion. Adverse events that were reported ≤ 1 day following a leukapheresis procedure in ≥ 5% of patients in controlled clinical trials included citrate toxicity (14.2%), oral paresthesia (12.6%), paresthesia (11.4%), and fatigue (8.3%).

Table 1 provides the frequency and severity of adverse events reported in ≥ 5% of patients in the PROVENGE group of randomized, controlled trials of men with prostate cancer. The population included 485 patients with metastatic castrate-resistant prostate cancer and 116 patients with non-metastatic androgen-dependent prostate cancer who were scheduled to receive 3 infusions of PROVENGE at approximately 2-week intervals. The population was age 40 to 91 years (median 70 years), and 90.6% of patients were Caucasian.

Table 1 Incidence of Adverse Events Occurring in ≥ 5% of Patients Randomized to PROVENGE
 | PROVENGE (N = 601) |  |  |  | Control* (N = 303)
 | All Grades n (%) |  | Grade 3-5 n (%) |  | All Grades n (%) |  | Grade 3-5 n (%)
Any Adverse Event | 591 (98.3) |  | 186 (30.9) |  | 291 (96.0) |  | 97 (32.0)
Chills | 319 (53.1) |  | 13 (2.2) |  | 33 (10.9) |  | 0 (0.0)
Fatigue | 247 (41.1) |  | 6 (1.0) |  | 105 (34.7) |  | 4 (1.3)
Fever | 188 (31.3) |  | 6 (1.0) |  | 29 (9.6) |  | 3 (1.0)
Back pain | 178 (29.6) |  | 18 (3.0) |  | 87 (28.7) |  | 9 (3.0)
Nausea | 129 (21.5) |  | 3 (0.5) |  | 45 (14.9) |  | 0 (0.0)
Joint ache | 118 (19.6) |  | 11 (1.8) |  | 62 (20.5) |  | 5 (1.7)
Headache | 109 (18.1) |  | 4 (0.7) |  | 20 (6.6) |  | 0 (0.0)
Citrate toxicity | 89 (14.8) |  | 0 (0.0) |  | 43 (14.2) |  | 0 (0.0)
Paresthesia | 85 (14.1) |  | 1 (0.2) |  | 43 (14.2) |  | 0 (0.0)
Vomiting | 80 (13.3) |  | 2 (0.3) |  | 23 (7.6) |  | 0 (0.0)
Anemia | 75 (12.5) |  | 11 (1.8) |  | 34 (11.2) |  | 7 (2.3)
Constipation | 74 (12.3) |  | 1 (0.2) |  | 40 (13.2) |  | 3 (1.0)
Pain | 74 (12.3) |  | 7 (1.2) |  | 20 (6.6) |  | 3 (1.0)
Paresthesia oral | 74 (12.3) |  | 0 (0.0) |  | 43 (14.2) |  | 0 (0.0)
Pain in extremity | 73 (12.1) |  | 5 (0.8) |  | 40 (13.2) |  | 1 (0.3)
Dizziness | 71 (11.8) |  | 2 (0.3) |  | 34 (11.2) |  | 0 (0.0)
Muscle ache | 71 (11.8) |  | 3 (0.5) |  | 17 (5.6) |  | 0 (0.0)
Asthenia | 65 (10.8) |  | 6 (1.0) |  | 20 (6.6) |  | 2 (0.7)
Diarrhea | 60 (10.0) |  | 1 (0.2) |  | 34 (11.2) |  | 3 (1.0)
Influenza-like illness | 58 (9.7) |  | 0 (0.0) |  | 11 (3.6) |  | 0 (0.0)
Musculoskeletal pain | 54 (9.0) |  | 3 (0.5) |  | 31 (10.2) |  | 3 (1.0)
Dyspnea | 52 (8.7) |  | 11 (1.8) |  | 14 (4.6) |  | 3 (1.0)
Edema peripheral | 50 (8.3) |  | 1 (0.2) |  | 31 (10.2) |  | 1 (0.3)
Hot flush | 49 (8.2) |  | 2 (0.3) |  | 29 (9.6) |  | 1 (0.3)
Hematuria | 46 (7.7) |  | 6 (1.0) |  | 18 (5.9) |  | 3 (1.0)
Muscle spasms | 46 (7.7) |  | 2 (0.3) |  | 17 (5.6) |  | 0 (0.0)
Hypertension | 45 (7.5) |  | 3 (0.5) |  | 14 (4.6) |  | 0 (0.0)
Anorexia | 39 (6.5) |  | 1 (0.2) |  | 33 (10.9) |  | 3 (1.0)
Bone pain | 38 (6.3) |  | 4 (0.7) |  | 22 (7.3) |  | 3 (1.0)
Upper respiratory tract infection | 38 (6.3) |  | 0 (0.0) |  | 18 (5.9) |  | 0 (0.0)
Insomnia | 37 (6.2) |  | 0 (0.0) |  | 22 (7.3) |  | 1 (0.3)
Musculoskeletal chest pain | 36 (6.0) |  | 2 (0.3) |  | 23 (7.6) |  | 2 (0.7)
Cough | 35 (5.8) |  | 0 (0.0) |  | 17 (5.6) |  | 0 (0.0)
Neck pain | 34 (5.7) |  | 3 (0.5) |  | 14 (4.6) |  | 2 (0.7)
Weight decreased | 34 (5.7) |  | 2 (0.3) |  | 24 (7.9) |  | 1 (0.3)
Urinary tract infection | 33 (5.5) |  | 1 (0.2) |  | 18 (5.9) |  | 2 (0.7)
Rash | 31 (5.2) |  | 0 (0.0) |  | 10 (3.3) |  | 0 (0.0)
Sweating | 30 (5.0) |  | 1 (0.2) |  | 3 (1.0) |  | 0 (0.0)
Tremor | 30 (5.0) |  | 0 (0.0) |  | 9 (3.0) |  | 0 (0.0)
* Control group received non-activated autologous peripheral blood mononuclear cells.

6.2 Postmarketing Experience

The following adverse reactions have been identified during post-approval use of PROVENGE. Because these reactions are reported voluntarily from a population of uncertain size, it is not always possible to reliably estimate their frequency or establish a causal relationship to drug exposure.

- Nervous system disorders: syncope, transient ischemic attack, strokes [see Warnings and Precautions (5.1, 5.3)]
- Vascular disorders: hypotension [see Warnings and Precautions (5.1)]
- Cardiovascular disorders: myocardial infarction [see Warnings and Precautions (5.3)]
- Thromboembolic disorders: deep venous thrombosis and pulmonary embolism [see Warnings and Precautions (5.2)]

8 USE IN SPECIFIC POPULATIONS

8.5 Geriatric

In controlled clinical trials, 72.9% of patients (438 of 601) in the PROVENGE group were ≥ 65 years of age. There were no apparent differences in the safety of PROVENGE between patients ≥ 65 years of age and younger patients.

In a survival analysis of the controlled clinical trials of PROVENGE in metastatic castrate-resistant prostate cancer, 78.3% of randomized patients (382 of 488) were ≥ 65 years of age. The median survival of patients in the PROVENGE group ≥ 65 years of age was 23.4 months (95% confidence interval 22.0, 27.1), compared with 17.3 months in the control group (95% confidence interval: 13.5, 21.5).

8.6 Race

In controlled clinical trials, 90.6% of patients were Caucasian, 5.8% were African American, and 3.7% were “Other”. Due to the low numbers of non-Caucasian patients in the trials, no conclusions can be made regarding the safety or efficacy of PROVENGE by race.

10 OVERDOSAGE

Each PROVENGE infusion comprises the maximum number of cells that can be manufactured from a single leukapheresis procedure. The number of cells in PROVENGE does not exceed the number of cells collected from the leukapheresis. There are no known instances of overdosage from either a single infusion or a full course of therapy with PROVENGE.

11 DESCRIPTION

PROVENGE (sipuleucel-T) is an autologous cellular immunotherapy available as a suspension for intravenous infusion. PROVENGE consists of autologous peripheral blood mononuclear cells, including antigen presenting cells (APCs), that have been activated during a defined culture period with a recombinant human protein, PAP-GM-CSF, consisting of prostatic acid phosphatase (PAP), an antigen expressed in prostate cancer tissue, linked to granulocyte-macrophage colony-stimulating factor (GM-CSF), an immune cell activator. Each dose of PROVENGE contains a minimum of 50 million autologous CD54^+ cells activated with PAP-GM-CSF, suspended in 250 mL of Lactated Ringer's Injection, USP.

The active components of PROVENGE are autologous APCs and PAP-GM-CSF. During culture, the recombinant antigen can bind to and be processed by APCs into smaller protein fragments. The recombinant antigen is designed to target APCs, and may help direct the immune response to PAP. Minimal residual levels of the intact PAP-GM-CSF are detectable in the final PROVENGE product.

The patient's peripheral blood mononuclear cells are obtained via a standard leukapheresis procedure approximately 3 days prior to the infusion date. Due to the autologous nature of PROVENGE, it is important that the patient and physician adhere to the personalized leukapheresis and infusion schedules.

The cellular composition of PROVENGE is dependent on the composition of cells obtained from the patient's leukapheresis. In addition to APCs, the final product contains T cells, B cells, natural killer (NK) cells, and other cells. The number of cells present and the cellular composition of each PROVENGE dose will vary.

The potency of PROVENGE is in part determined by measuring the increased expression of the CD54 molecule, also known as ICAM-1, on the surface of APCs after culture with PAP-GM-CSF. CD54 is a cell surface molecule that plays a role in the immunologic interactions between APCs and T cells, and is considered a marker of immune cell activation.

In-process and final sterility tests are initiated prior to shipping, but the final results are not available for up to 7 days. PROVENGE is released for shipping based on acceptable results from 2-day incubation of the in-process sterility test.

12 CLINICAL PHARMACOLOGY

12.1 Mechanism of Action

PROVENGE is classified as an autologous cellular immunotherapy. While the precise mechanism of action is unknown, PROVENGE is designed to induce an immune response targeted against PAP, an antigen expressed in most prostate cancers. During ex vivo culture with PAP-GM-CSF, APCs take up and process the recombinant target antigen into small peptides that are then displayed on the APC surface.

In Study 1, 237 out of the 512 patients randomized were evaluated for the development of humoral and T cell immune responses (proliferative and gamma-interferon (γIFN) ELISPOT) to the target antigens at Baseline, and at Weeks 6, 14, and 26. Antibody (IgM and IgG) responses against PAP-GM-CSF and PAP antigen alone were observed through the follow-up period in the PROVENGE group. Neutralizing antibody responses to GM-CSF were transient. T cell proliferative and γIFN ELISPOT responses to PAP-GM-CSF fusion protein were observed in cells collected from peripheral blood of patients through the follow-up period in the PROVENGE treatment group but not in controls. In some patients a response to PAP antigen alone was observed. No conclusions could be made regarding the clinical significance of the observed immune responses.

14 CLINICAL STUDIES

The effect of PROVENGE on patients with metastatic castrate-resistant (hormone-refractory) prostate cancer was studied in three similar randomized, double-blind, placebo-controlled, multicenter trials. Following randomization, patients from both treatment groups underwent a series of 3 leukapheresis procedures (at approximately Weeks 0, 2, and 4). Each leukapheresis was followed approximately 3 days later by infusion of PROVENGE or control. The control was autologous peripheral blood mononuclear cells that had not been activated [ see Description (11)]. Following disease progression, patients were treated at the physician's discretion with other anti-cancer interventions.

Study 1

Study 1 was a randomized, double-blind, placebo-controlled, multicenter trial in patients with asymptomatic or minimally symptomatic metastatic castrate-resistant (hormone-refractory) prostate cancer. Eligible patients had metastatic disease in the soft tissue and/or bone with current or historical evidence of disease progression concomitant with surgical or medical castration, as evidenced by progression of serum Prostate Specific Antigen (PSA) and/or bone or soft tissue disease. Exclusion criteria included visceral (liver, lung, or brain) metastases, moderate to severe prostate cancer-related pain, and use of narcotics for cancer-related pain.

A total of 512 patients were randomized in a 2:1 ratio to receive PROVENGE (n=341) or control (n=171). The median age was 71, and 90% of the patients were Caucasian. Thirty-five percent of patients had undergone radical prostatectomy, 54% had received local radiotherapy, and 82% had received combined androgen blockade. All patients had baseline testosterone levels < 50 ng/mL. Forty-eight percent of patients were receiving bisphosphonates, and 18% had received prior chemotherapy, including docetaxel. Eighty-two percent of patients had an ECOG performance status of 0; 58% had primary Gleason scores of four or more; 44% had bone and soft tissue disease; 48% had bone-only disease; 7% had soft tissue-only disease; and 43% had greater than ten bony metastases.

Supportive Studies

Study 2 was a randomized, double-blind, placebo-controlled, multicenter trial in patients with metastatic castrate-resistant prostate cancer and no cancer-related pain. The primary endpoint was time to disease progression; analysis of the primary endpoint did not reach statistical significance. All patients were to be followed for survival; however, the survival analysis was not pre-specified.

Summary of Study Results

Figure 1 and Table 2 present overall survival results observed in two randomized, Phase 3 studies of PROVENGE in men with metastatic castrate-resistant prostate cancer. The survival findings were consistent across multiple subgroups. Analyses of time to disease progression did not meet statistical significance in any Phase 3 study of PROVENGE.

Figure 1 Kaplan-Meier Overall Survival Curve for Study 1

Table 2 Summary of Overall Survival (All Patients as Randomized)
 | Study 1 |  | Study 2
 | PROVENGE (N=341) | Control (N=171) | PROVENGE(N=82) | Control (N=45)
Overall Survival
Median, months (95% CI) | 25.8 (22.8, 27.7) | 21.7 (17.7, 23.8) | 25.9 (20.0, 32.4) | 21.4 (12.3, 25.8)
Hazard Ratio (95% CI) | 0.775a (0.614, 0.979) |  | 0.586b (0.388, 0.884)
p-value | 0.032a |  | 0.010c
a Hazard ratio and p-value based on the Cox Model adjusted for PSA (ln) and LDH (ln) and stratified by bisphosphonate use, number of bone metastases, and primary Gleason grade.
b Hazard ratio based on the unadjusted Cox Model (not pre-specified).
c p-value based on a log-rank test (not pre-specified).
Abbreviations: CI = confidence interval.

16 HOW SUPPLIED/STORAGE AND HANDLING

PROVENGE is a 250 mL suspension containing a minimum of 50 million autologous CD54^+ cells activated with PAP-GM-CSF in Lactated Ringer's Injection, USP. It is supplied in a sealed infusion bag, labeled for the specific recipient.

NDC 30237-8900-6: One bag individually packed in a carton.

PROVENGE is shipped directly to the infusing provider in a cardboard shipping box with a special insulated polyurethane container inside. The insulated container and gel packs within the container are designed to maintain the appropriate transportation and storage temperature of PROVENGE until infusion.

- Upon receipt, open the outer cardboard shipping box to verify the product and patient-specific labels located on the top of the insulated container.
- Do not remove the insulated container from the shipping box, or open the lid of the insulated container, until the patient is ready for infusion.

17 PATIENT COUNSELING INFORMATION

- Advise the patient to read the FDA-approved patient labeling (Patient Information).
- Inform the patient or caregiver about the following:
  - The recommended course of therapy for PROVENGE is 3 complete doses. Each infusion of PROVENGE is preceded by a leukapheresis procedure approximately 3 days prior. It is important to maintain all scheduled appointments and arrive at each appointment on time because the leukapheresis and infusions must be appropriately spaced and the PROVENGE expiration time must not be exceeded.
  - If the patient is unable to receive an infusion of PROVENGE, the patient will need to undergo an additional leukapheresis procedure if the treatment is to be continued.
  - Counsel the patient on the importance of adhering to preparation instructions for the leukapheresis procedure, the possible side effects of leukapheresis, and post-procedure care.
  - If the patient does not have adequate peripheral venous access to accommodate the leukapheresis procedure and infusion of PROVENGE, inform the patient about the need for a central venous catheter. Counsel the patient on the importance of catheter care. Instruct the patient to tell their doctor if they are experiencing fevers or any swelling or redness around the catheter site, because these symptoms could be signs of an infected catheter.
  - Report signs and symptoms of acute infusion reactions such as fever, chills, fatigue, breathing problems, dizziness, high blood pressure, low blood pressure, lightheadedness, nausea, vomiting, headache, or muscle aches.
  - Report any symptoms suggestive of a cardiac arrhythmia.
  - Report any symptoms suggestive of cardiac ischemia.
  - Report any symptoms suggestive of cerebral ischemia.
  - Report any symptoms suggestive of deep vein thrombosis.
  - Report any symptoms suggestive of pulmonary embolism.
  - Inform their doctor if they are taking immunosuppressive agents.

For more information, please call the toll-free number: 1-877-336-3736.

Dendreon Pharmaceuticals LLC
Seal Beach, CA 90740
LBS-76022.04

Rev. 07/2017

PATIENT INFORMATION

PROVENGE® (sipuleucel-T)

This leaflet is designed to help you understand treatment with PROVENGE (pronounced PROH-venj). The more you understand your treatment, the better you will be able to participate in your care. This leaflet does not take the place of talking with your doctor or healthcare professional about your medical condition or your treatment. If you have any questions, speak with your doctor.

What is PROVENGE?

PROVENGE is a prescription medicine that is used to treat certain patients with advanced prostate cancer. PROVENGE is made from your own immune cells.

What should I tell my doctor before getting PROVENGE?

Tell your doctor about all your medical problems, including:

- heart problems
- lung problems
- history of stroke

Tell your doctor about all the medicines you take, including prescription and nonprescription drugs, vitamins, and dietary supplements.

How will I get PROVENGE?

Since PROVENGE is made from your own immune cells, your cells will be collected approximately 3 days before each scheduled infusion of PROVENGE. You will need to go to a cell collection center for this collection. The collection is called “leukapheresis” (pronounced loo-kuh-fuh-REE-sis). Your collected cells are sent to a manufacturing center where they are mixed with a protein to make them ready for your infusion.

You will get PROVENGE in 3 intravenous infusions (put into your veins), about 2 weeks apart. Each infusion takes about 60 minutes. Following each infusion, you will be monitored for at least 30 minutes.

Your doctor will give you a schedule for your cell collection and infusion appointments. It is very important that you arrive on time for your appointments. If you miss an appointment and cannot be infused, your PROVENGE dose will not be usable. Your doctor will work with you to schedule a new appointment at the cell collection center. You may also get a new infusion appointment.

What are the possible or reasonably likely side effects of PROVENGE?

The most common side effects of PROVENGE include:

- chills
- fatigue
- fever
- back pain

- nausea
- joint ache
- headache

PROVENGE infusion can cause serious reactions.

Tell your doctor right away if

- you have breathing problems, chest pains, racing heart or irregular heartbeats, high or low blood pressure, dizziness, fainting, nausea, or vomiting after getting PROVENGE. Any of these may be signs of heart or lung problems.
- you develop numbness or weakness on one side of the body, decreased vision in one eye or difficulty speaking. Any of these may be signs of a stroke.
- you develop symptoms of thrombosis which may include: pain and/or swelling of an arm or leg with warmth over the affected area, discoloration of an arm or leg, unexplained shortness of breath, chest pain that worsens on deep breathing.
- you get a fever over 100ºF, or redness or pain at the infusion or collection sites. Any of these may be signs of infection.

Tell your doctor about any side effect that concerns you or does not go away.

These are not all the possible side effects of PROVENGE treatment. For more information, talk with your doctor.

What are the ingredients in PROVENGE?

The active components of PROVENGE are your own immune cells mixed with the other active component, a protein designed to produce an immune response to prostate cancer. The product is suspended in an infusion solution called Lactated Ringer's Injection, USP, an inactive ingredient.

If you would like more information about PROVENGE, talk with your doctor. You can also call toll-free 1-877-336-3736 or visit www.PROVENGE.com.

Dendreon Pharmaceuticals LLC
Seal Beach, CA 90740
LBS-76022.04
Rev. 07/2017

Principal Display Panel – Carton Label

NDC 30237-8900-6

sipuleucel-T

PROVENGE®

RX ONLY FOR AUTOLOGOUS USE ONLY

No U.S. standard of potency

CONTENTS: A minimum of 50 million autologous CD54^+ cells activated with PAP-GM-CSF and suspended in Lactated Ringer's Injection, USP.

Manufactured by:

Dendreon Pharmaceuticals LLC Seal Beach, CA 90740

Phone: 877-256-4545

U.S. Lic. # 1749

No preservatives. Gently mix and re-suspend the contents of the bag. 76082.04

One autologous dose for infusion. See package insert for full prescribing information and instructions for administration.

Principal Display Panel – Bag Label

NDC 30237-8900-5

sipuleucel-T

PROVENGE®

RX ONLY FOR AUTOLOGOUS USE ONLY

No U.S. standard of potency

CONTENTS: A minimum of 50 million autologous CD54^+ cells activated with PAP-GM-CSF and suspended in Lactated Ringer's Injection, USP.

Manufactured by:

Dendreon Pharmaceuticals LLC Seal Beach, CA 90740

Phone: 877-256-4545

U.S. Lic. # 1749

No preservatives. Gently mix and re-suspend the contents of the bag. 000074.01

One autologous dose for infusion. See package insert for full prescribing information and instructions for administration.

Package Label 2

sipuleucel-T 250 mL Lot XXXXXX-X

Store Refrigerated 2-8°C DO NOT FREEZE

Expiration Date: DD-MMM-YYYY

Expiration Time: XX:XX Time Zone:

First Name MI:

Last Name:

Date of Birth: DD-MMM-YYYY

NOT EVALUATED FOR INFECTIOUS SUBSTANCES